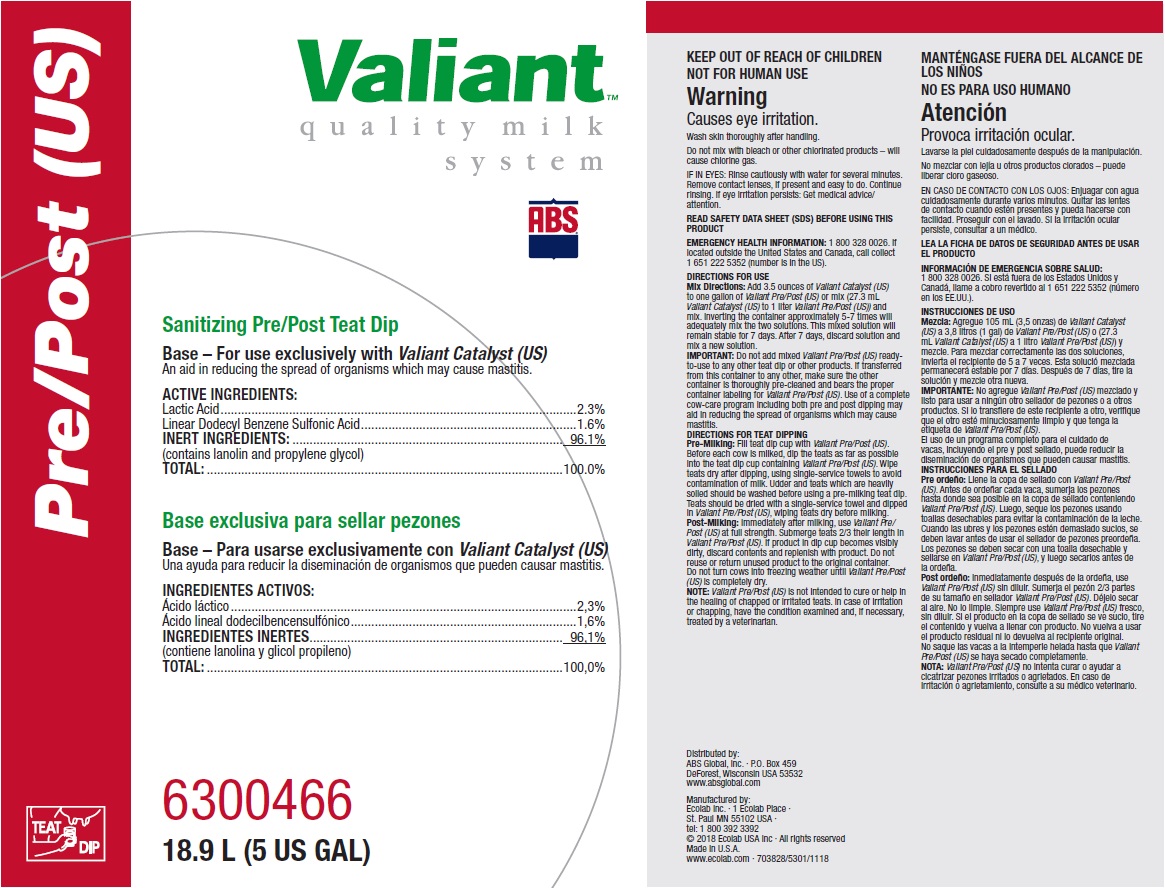 DRUG LABEL: Valiant Pre/Post
NDC: 59282-102 | Form: SOLUTION
Manufacturer: ABS Global Inc.
Category: animal | Type: OTC ANIMAL DRUG LABEL
Date: 20230803

ACTIVE INGREDIENTS: LACTIC ACID 23 mg/1 mL; DODECYLBENZENESULFONIC ACID 16 mg/1 mL
INACTIVE INGREDIENTS: PROPYLENE GLYCOL; PEG-75 LANOLIN; WATER

KEEP OUT OF REACH OF CHILDREN

NOT FOR HUMAN USE

Warning

Causes eye irritation.

Wash skin thoroughly after handling.

Do not mix with bleach or other chlorinated products – will cause chlorine gas.

IF IN EYES: Rinse cautiously with water for several minutes. Remove contact lenses, if present and easy to do. Continue rinsing. If eye irritation persists: Get medical advice/ attention.

VETERINARY INDICATIONS

DIRECTIONS FOR USE

Mix Directions: Add 3.5 ounces of Valiant Catalyst (US) to one gallon of Valiant Pre/Post (US) or mix (27.3 mL Valiant Catalyst (US) to 1 liter Valiant Pre/Post (US)) and mix. Inverting the container approximately 5-7 times will adequately mix the two solutions. This mixed solution will remain stable for 7 days. After 7 days, discard solution and mix a new solution.

IMPORTANT: Do not add mixed Valiant Pre/Post (US) ready-to-use to any other teat dip or other products. If transferred from this container to any other, make sure the other container is thoroughly pre-cleaned and bears the proper container labeling for Valiant Pre/Post (US). Use of a complete cow-care program including both pre and post dipping may aid in reducing the spread of organisms which may cause mastitis.

DIRECTIONS FOR TEAT DIPPING

Pre-Milking: Fill teat dip cup with Valiant Pre/Post (US). Before each cow is milked, dip the teats as far as possible into the teat dip cup containing Valiant Pre/Post (US). Wipe teats dry after dipping, using single-service towels to avoid contamination of milk. Udder and teats which are heavily soiled should be washed before using a pre-milking teat dip. Teats should be dried with a single-service towel and dipped in Valiant Pre/Post (US), wiping teats dry before milking.

Post-Milking: Immediately after milking, use Valiant Pre/Post (US) at full strength. Submerge teats 2/3 their length in Valiant Pre/Post (US). If product in dip cup becomes visibly dirty, discard contents and replenish with product. Do not reuse or return unused product to the original container.

Do not turn cows into freezing weather until Valiant Pre/Post (US) is completely dry.

NOTE: Valiant Pre/Post (US) is not intended to cure or help in the healing of chapped or irritated teats. In case of irritation or chapping, have the condition examined and, if necessary, treated by a veterinarian.

OTHER SAFETY INFORMATION

READ SAFETY DATA SHEET (SDS) BEFORE USING THIS PRODUCT

EMERGENCY HEALTH INFORMATION: 1 800 328 0026. If located outside the United States and Canada, call collect 1 651 222 5352 (number is in the US).

Principal display panel and representative container

Valiant

Quality milk system

ABS

Pre/Post (US)

Sanitizing Pre/Post Teat Dip

Base – For use exclusively with Valiant Catalyst (US)

An aid in reducing the spread of organisms which may cause mastitis.

ACTIVE INGREDIENTS:

Lactic Acid.........................................................................................................2.3%

Linear Dodecyl Benzene Sulfonic Acid................................................................1.6%

INERT INGREDIENTS:................................................................................ 96.1%

(contains lanolin and propylene glycol)

TOTAL:.........................................................................................................100.0%

6300466

18.9 L (5 US GAL)

Distributed by:

ABS Global, Inc. · P.O. Box 459

DeForest, Wisconsin USA 53532

www.absglobal.com

Manufactured by:

Ecolab Inc. ∙ 1 Ecolab Place ∙

St. Paul MN 55102 USA ·

tel: 1 800 392 3392

© 2018 Ecolab USA Inc · All rights reserved

Made in U.S.A.

www.ecolab.com

703828/5301/1118